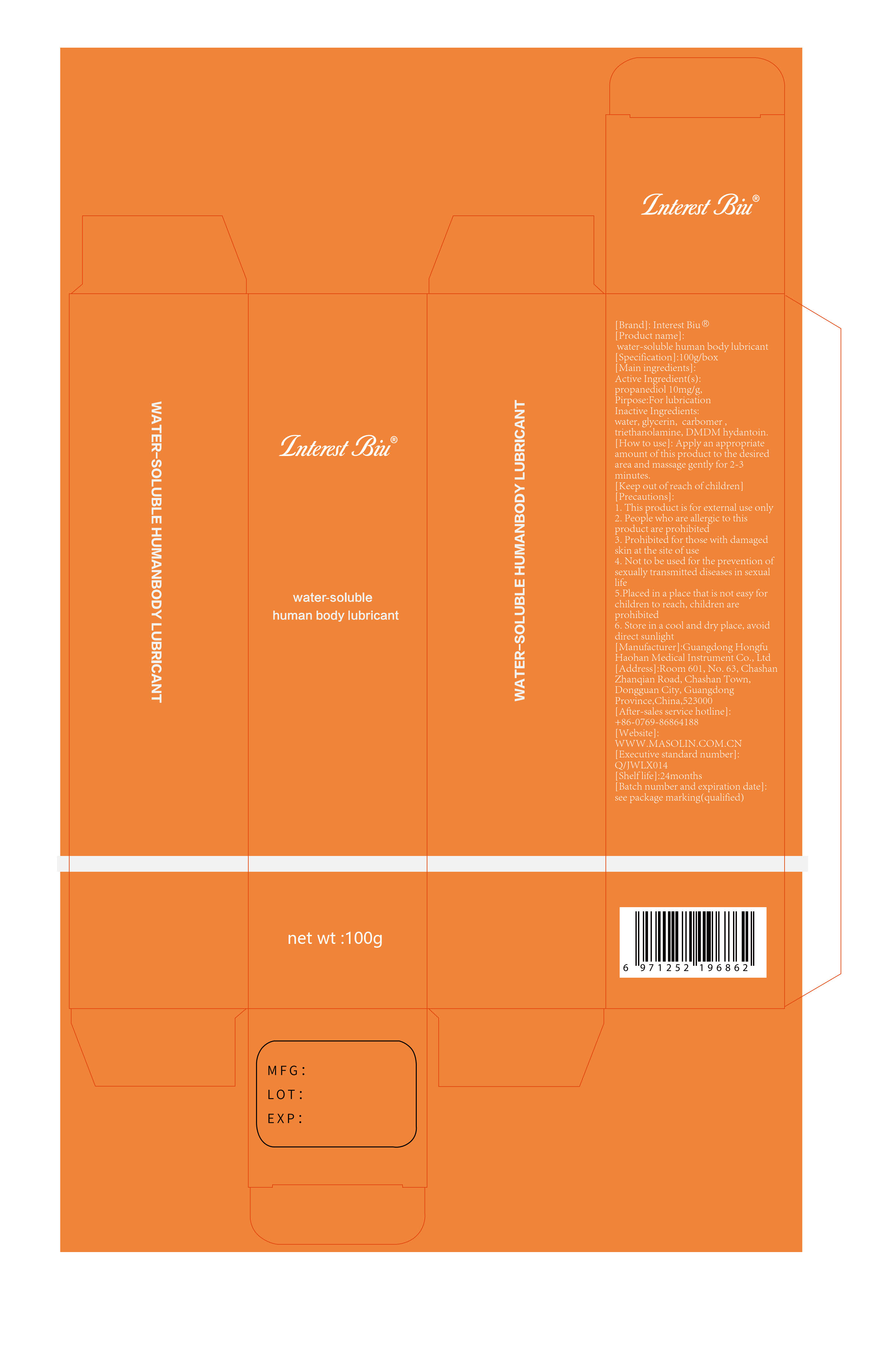 DRUG LABEL: water-soluble human body lubricant
NDC: 82408-501 | Form: LOTION
Manufacturer: Guangdong Hongfu Haohan Medical Instrument Co., Ltd.
Category: homeopathic | Type: HUMAN OTC DRUG LABEL
Date: 20211202

ACTIVE INGREDIENTS: PROPANEDIOL 10 mg/1 g
INACTIVE INGREDIENTS: CARBOMER HOMOPOLYMER TYPE C (ALLYL PENTAERYTHRITOL CROSSLINKED); GLYCERIN; TROLAMINE; WATER; DMDM HYDANTOIN

water-soluble human body lubricant, 100g

Active ingredient

Propanediol 1% w/w

Purpose

For lubrication

Precautions

1. This product is for external use only
2. People who are allergic to this product are prohibited
3. Prohibited for those with damaged skin at the site of use
4. Not to be used for the prevention of sexually transmitted diseases in sexual life
5. Placed in a place that is not easy for children to reach, children are prohibited
6. Store in a cool and dry place, avoid direct sunlight

When using

Prohibited for those with damaged skin at the site of use

Do not use

1. People who are allergic to this product are prohibited
2. Prohibited for those with damaged skin at the site of use
3. Not to be used for the prevention of sexually transmitted diseases in sexual life

Keep out of reach of children

Placed in a place that is not easy for children to reach, children are prohibited

How to use

Sexual lubrication.

Apply an appropriate amount of this product to the desired area and massage gently for 2-3 minutes.

How to use

Apply an appropriate amount of this product to the desired area and massage gently for 2-3 minutes.

Inactive ingredients

water, glycerin, carbomer, triethanolamine, DMDM hydantoin.

After-sales service hotline:

+86-0769-86864188